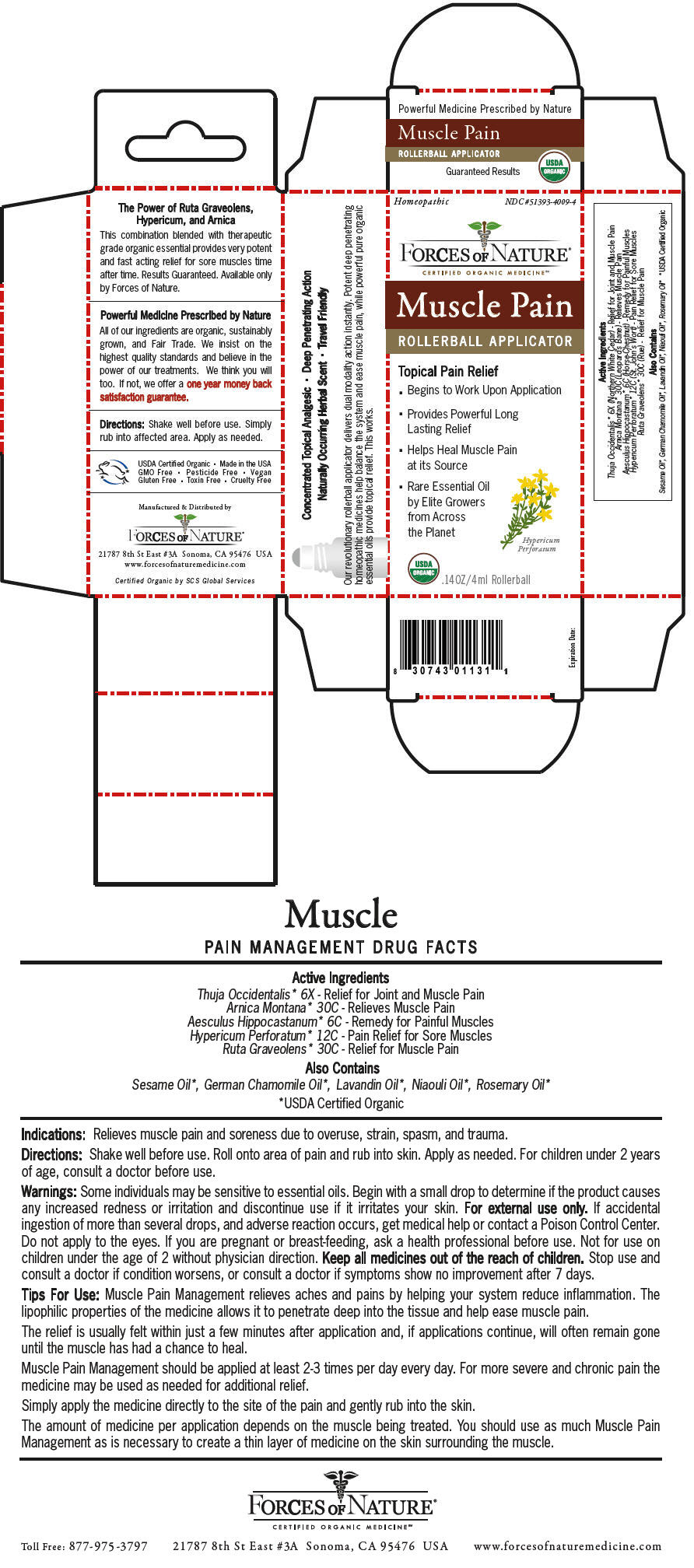 DRUG LABEL: Muscle Pain 
NDC: 51393-4009 | Form: SOLUTION/ DROPS
Manufacturer: Forces of Nature
Category: homeopathic | Type: HUMAN OTC DRUG LABEL
Date: 20221025

ACTIVE INGREDIENTS: ARNICA MONTANA WHOLE 30 [hp_C]/1000 mL; Horse Chestnut 6 [hp_C]/1000 mL; HYPERICUM PERFORATUM WHOLE 12 [hp_C]/1000 mL; Ruta Graveolens Flowering Top 30 [hp_C]/1000 mL; Thuja Occidentalis Leafy Twig 6 [hp_X]/1000 mL
INACTIVE INGREDIENTS: MELALEUCA QUINQUENERVIA LEAF OIL; Chamomile Flower Oil; Lavandin Oil; Rosemary Oil; Sesame Oil

Muscle Pain
Pain Management

DRUG FACTS

ACTIVE INGREDIENT

PURPOSE

Active Ingredients

Thuja Occidentalis [USDA Certified Organic] 6X - Relief for Joint and Muscle Pain

Arnica Montana 30C - Relieves Muscle Pain

Aesculus Hippocastanum 6C - Remedy for Painful Muscles

Hypericum Perforatum 12C - Pain Relief for Sore Muscles

Ruta Graveolens 30C - Relief for Muscle Pain

Also Contains

Sesame Oil, German Chamomile Oil, Lavandin Oil, Niaouli Oil, Rosemary Oil

Indications

Relieves muscle pain and soreness due to overuse, strain, spasm, and trauma.

Directions

Shake well before use. Roll onto area of pain and rub into skin. Apply as needed. For children under 2 years of age, consult a doctor before use.

Warnings

Some individuals may be sensitive to essential oils. Begin with a small drop to determine if the product causes any increased redness or irritation and discontinue use if it irritates your skin. For external use only. If accidental ingestion of more than several drops, and adverse reaction occurs, get medical help or contact a Poison Control Center. Do not apply to the eyes. If you are pregnant or breast-feeding, ask a health professional before use. Not for use on children under the age of 2 without physician direction.

KEEP OUT OF REACH OF CHILDREN

Keep all medicines out of the reach of children. Stop use and consult a doctor if condition worsens, or consult a doctor if symptoms show no improvement after 7 days.

Tips For Use

Muscle Pain Management relieves aches and pains by helping your system reduce inflammation. The lipophilic properties of the medicine allows it to penetrate deep into the tissue and help ease muscle pain.

The relief is usually felt within just a few minutes after application and, if applications continue, will often remain gone until the muscle has had a chance to heal.

Muscle Pain Management should be applied at least 2-3 times per day every day. For more severe and chronic pain the medicine may be used as needed for additional relief.

Simply apply the medicine directly to the site of the pain and gently rub into the skin.

The amount of medicine per application depends on the muscle being treated. You should use as much Muscle Pain Management as is necessary to create a thin layer of medicine on the skin surrounding the muscle.

Manufactured & Distributed by

FORCES OF NATURE®

21787 8th St East #3A Sonoma, CA 95476 USA

PRINCIPAL DISPLAY PANEL - 4 ml Bottle Carton

Homeopathic
NDC #51393-4009-4

FORCES OF NATURE®

CERTIFIED ORGANIC MEDICINE℠

Muscle Pain

ROLLERBALL APPLICATOR

Topical Pain Relief

- Begins to Work Upon Application
- Provides Powerful Long
  Lasting Relief
- Helps Heal Muscle Pain
  at its Source
- Rare Essential Oil
  by Elite Growers
  from Across
  the Planet

Hypericum
Perforatum

USDA
ORGANIC

.14OZ/4ml Rollerball